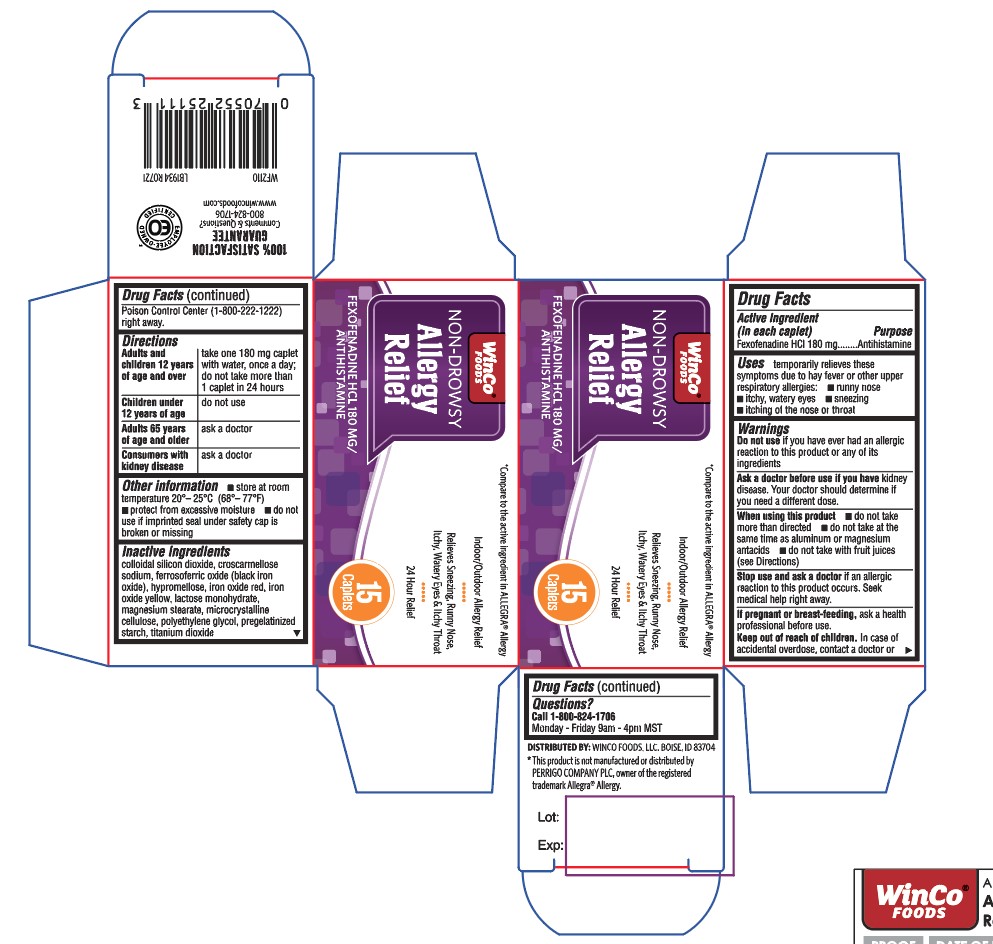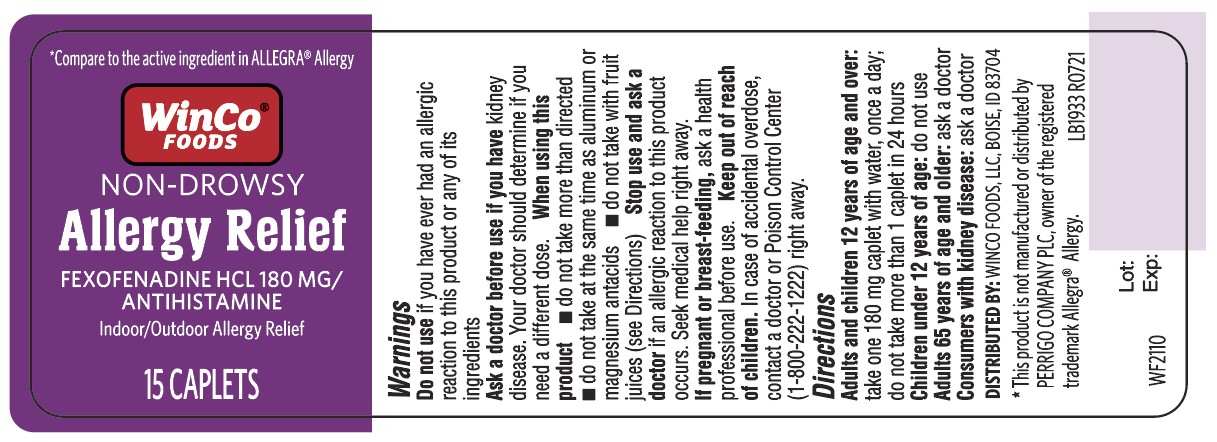 DRUG LABEL: Allergy Relief
NDC: 67091-386 | Form: CAPSULE
Manufacturer: WinCo Foods
Category: otc | Type: HUMAN OTC DRUG LABEL
Date: 20220106

ACTIVE INGREDIENTS: FEXOFENADINE HYDROCHLORIDE 180 mg/1 1
INACTIVE INGREDIENTS: SILICON DIOXIDE; CROSCARMELLOSE SODIUM; FERROSOFERRIC OXIDE; HYPROMELLOSE, UNSPECIFIED; FERRIC OXIDE RED; FERRIC OXIDE YELLOW; LACTOSE MONOHYDRATE; MAGNESIUM STEARATE; MICROCRYSTALLINE CELLULOSE; POLYETHYLENE GLYCOL, UNSPECIFIED; STARCH, CORN; TITANIUM DIOXIDE

413 - Allergy Relief

Active ingredient(s)

Fexofenadine HCl 180 mg

Purpose

Antihistamine

Use(s)

temporarily relieves these symptoms due to hay fever or other upper respiratory
allergies:

- runny nose
- itchy, watery eyes
- sneezing
- itching of the nose or throat

Warnings

Do not use

if you have ever had an allergic reaction to this product or any of its ingredients

Ask a doctor before use if

kidney disease. Your doctor should determine if you need a different dose.

When using this product

- do not take more than directed
- do not take at the same time as aluminum or magnesium antacids
- do not take with fruit juices (see Directions)

Stop use and ask a doctor if

an allergic reaction to this product occurs. Seek medical help right away.

Pregnancy/Breastfeeding

ask a health professional before use.

Keep out of reach of children

In case of accidental overdose, contact a doctor or Poison Control Center (1-800-222-1222) right away.

Directions

Adults and children 12 years of age and over take one 180 mg caplet with water, once a day; do not take more than 1 caplet in 24 hours

Children under 12 years of age do not use

Adults 65 years of age and older ask a doctor

Consumers with kidney disease ask a doctor

Other information

- store at room temperature 20°– 25°C (68°– 77°F)

- protect from excessive moisture

- do not use if imprinted seal under safety cap is broken or missing

Inactive ingredients

colloidal silicon dioxide, croscarmellose sodium, ferrosoferric oxide (black iron oxide),
hypromellose, iron oxide red, iron oxide yellow, lactose monohydrate, magnesium stearate,
microcrystalline cellulose, polyethylene glycol, pregelatinized starch, titanium dioxide

Questions

Call 1-800-824-1706 Monday - Friday 9AM - 4PM MST

Principal Display Panel

Allergy Relief
Allergy Relief